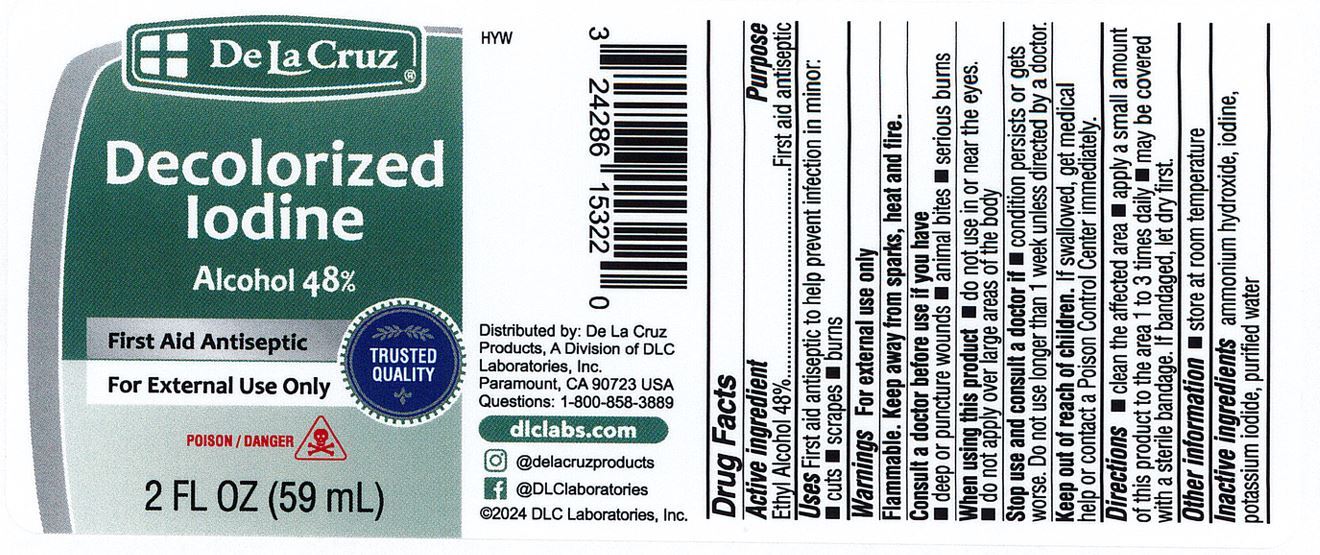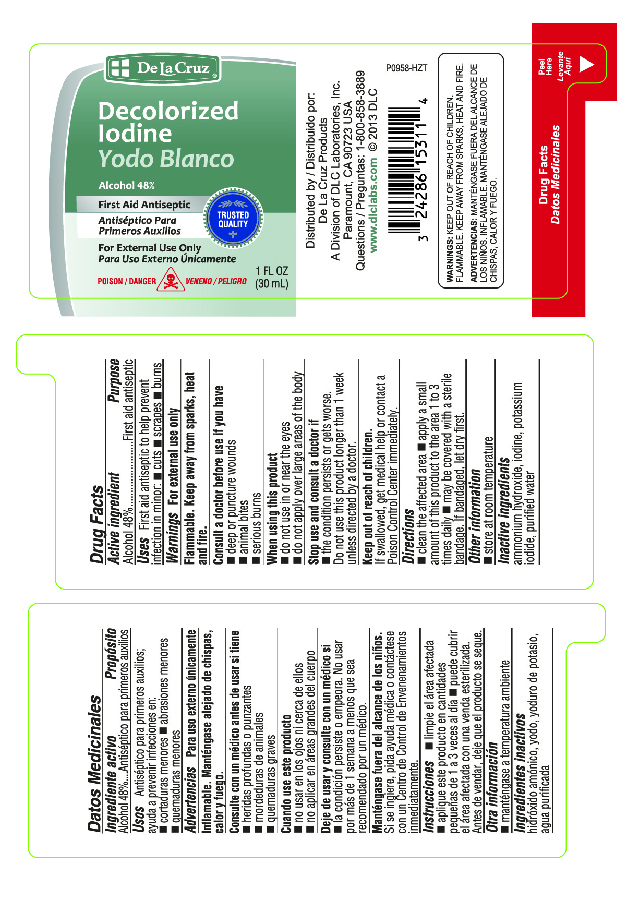 DRUG LABEL: De La Cruz Decolorized Iodine
NDC: 24286-1529 | Form: LIQUID
Manufacturer: DLC Laboratories, Inc.
Category: otc | Type: HUMAN OTC DRUG LABEL
Date: 20241218

ACTIVE INGREDIENTS: ALCOHOL 0.45 mL/1 mL
INACTIVE INGREDIENTS: AMMONIA; IODINE; POTASSIUM IODIDE; WATER

De La Cruz Decolorized Iodine

Drug Facts

Active Ingredients

Alcohol 45 % denatured with ammonia, Ammonium and Potassium Iodides.

Purpose

Antiseptic

Uses

First aid to help prevent infection in minor cuts, scrapes and burns.

Warnings

For external use only.

Ask a doctor before use if you have

deep or puncture wounds, animal bites, serious burns.

Stop use and ask a doctor if:

The condition persists or gets worse, or if using this product for longer than 1 week.

When using this product:

Do not use in the eyes. If contact occurs, flush with large amounts of water while lifting upper and lower lids. Do not apply over large areas of the body.

Keep out of the reach of children.

In case of acidental ingestion give milk, then give a starch solution made by mixing two tablespoonfools of cornstarch or flour to a pint of water. contact a poison Control Center immediately.

Directions

Clean the affected area. Aply a small amount to the affected area 1 to 3 times daily. May be covered with a sterile bandage. If bandaged, let it dry first.

Inactive Ingredient:

Purified Water

Pther Information:

Will stain skin and clothing